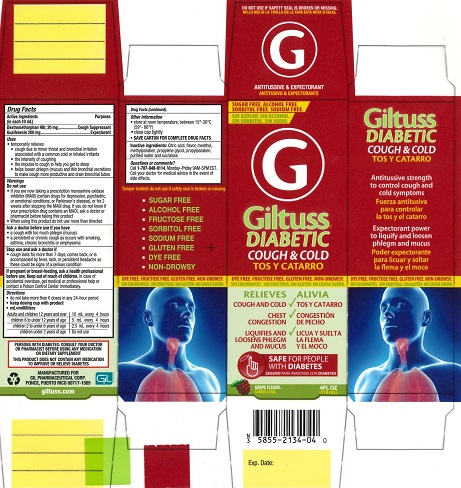 DRUG LABEL: Giltuss Diabetic

NDC: 58552-134 | Form: SOLUTION
Manufacturer: Gil Pharmaceutical Corp
Category: otc | Type: HUMAN OTC DRUG LABEL
Date: 20251009

ACTIVE INGREDIENTS: GUAIFENESIN 200 mg/10 mL; DEXTROMETHORPHAN HYDROBROMIDE 20 mg/10 mL
INACTIVE INGREDIENTS: PROPYLPARABEN; ANHYDROUS CITRIC ACID; METHYLPARABEN; MENTHOL; WATER; PROPYLENE GLYCOL; SUCRALOSE

Giltuss Diabetic Cough and Cold

Drug Facts

Active ingredients (in each 10 mL)

Dextromethorphan HBr, 20 mg

Guaifenesin 200 mg

Purposes

Cough Suppressant

Expectorant

Uses

- temporarily relieves
- cough due to minor throat and bronchial irritation associated with a common cold or inhaled irritants
- the intensity of coughing
- the impulse to cough to help you get to sleep
- helps loosen phlegm (mucus) and thin bronchial secretions to make coughs more productive and drain bronchial tubes

Warnings

Do not use

- if you are now taking a prescription monoamine oxidase inhibitor (MAOI) (certain drugs for depression, psychiatric or emotional conditions, or Parkinson's disease), or for 2 weeks after stopping the MAOl drug. If you do not know if your prescription drug contains an MAOI, ask a doctor or pharmacist before taking this product.

When using this product do not use more than directed

Ask a doctor before use if you have

- a cough with too much phlegm (mucus)
- a persistent or chronic cough as occurs with smoking, asthma, chronic bronchitis or emphysema

Stop use and ask a doctor if

- cough lasts more than 7 days, comes back, or is accompanied by fever, rash or headache that lasts as these could be signs of a serious condition.

PREGNANCY OR BREAST FEEDING

If pregnant or breast-feeding, ask a health professional before use.

Keep out of reach of children.In case of accidental overdose, get medical or professional help or contact a Poison Control Center immediately.

Directions

- do not take more than 6 doses in any 24-hour period
- keep dosing cup with product
- mL = milliliters

Adults and children 12 years and over | 10 mL every 4 hours
children 6 to under 12 years of age | 5 mL every 4 hours
children 2 to under 6 years of age | 2.5 mL every 4 hours
children under 2 years of age | Do not use

Other information

- store at room temperature, between 15°- 30°C (59°- 86°F)
- close cap tightly
- SAVE CARTON FOR COMPLETE DRUG FACTS

INACTIVE INGREDIENT

Inactive ingredients:Citric acid, flavor, menthol, methylparaben, propylene glycol, propylparaben, purified water and sucralose.

Questions or comments?

Call 1-787-848-9114, Monday-Friday 9AM-5PM EST.

Call your doctor for medical advice in the event of side effects.

MANUFACTURED FOR

GIL PHARMACEUTICAL CORP.

PONCE, PUERTO RICO 00717-1565

OTHER SAFETY INFORMATION

Tamper evident: do not use if safety seal is broken or missing.

PERSONS WITH DIABETES: CONSULT YOUR DOCTOR OR PHARMACIST BEFORE USING ANY MEDICATION OR DIETARY SUPPLEMENT

THIS PRODUCT DOES NOT CONTAIN ANY MEDICATION TO IMPROVE OR RELIEVE DIABETES

PACKAGE LABEL

Giltuss® DIABETIC

COUGH & COLD

RELIEVES

- COUGH AND COLD
- CHEST CONGESTION
- LIQUIFIES AND LOOSENS PHLEGM AND MUCUS

SAFE FOR PEOPLE WITH DIABETES

GRAPE FLAVOR

4 FL OZ (118 mL)